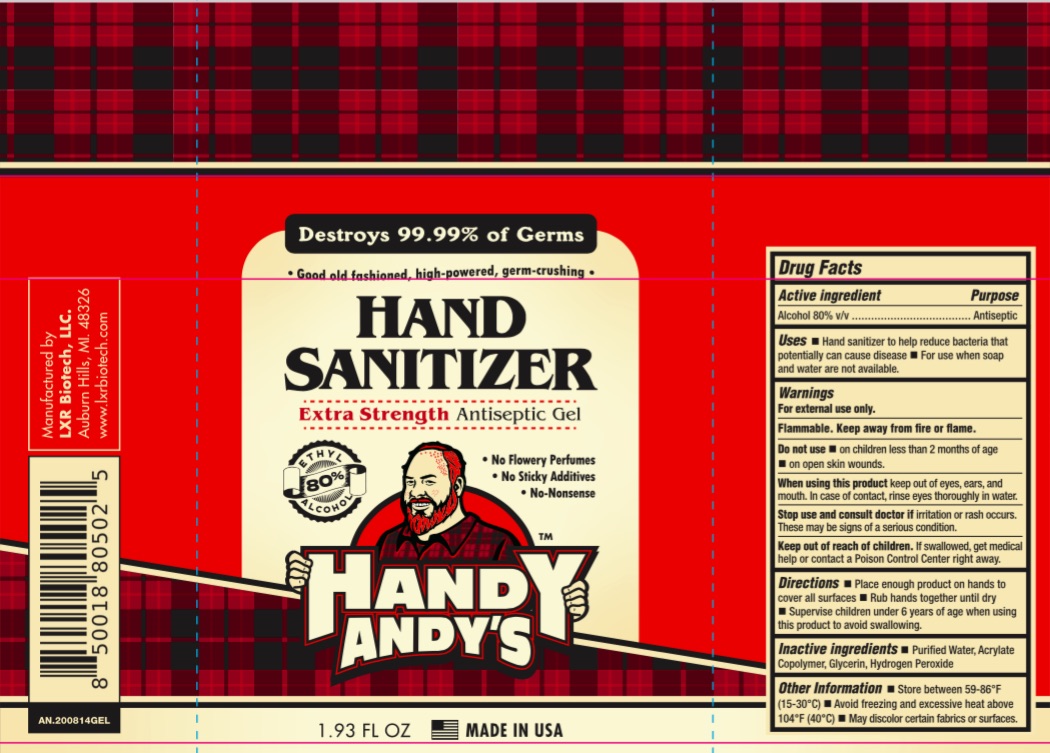 DRUG LABEL: Handy Andys
NDC: 78299-142 | Form: GEL
Manufacturer: LXR Biotech LLC
Category: otc | Type: HUMAN OTC DRUG LABEL
Date: 20220127

ACTIVE INGREDIENTS: ALCOHOL 80 mL/100 mL
INACTIVE INGREDIENTS: GLYCERIN; HYDROGEN PEROXIDE; WATER; BUTYL ACRYLATE/METHYL METHACRYLATE/METHACRYLIC ACID COPOLYMER (18000 MW)

LXR-Handy Andy Sanitizer Gel

Active Ingredient(s)

Alcohol 80% v/v. Purpose: Antiseptic

Purpose

Antiseptic, Hand Sanitizer

Use

Hand Sanitizer to help reduce bacteria that potentially can cause disease. For use when soap and water are not available.

Warnings

For external use only. Flammable. Keep away from heat or flame

Do not use

- in children less than 2 months of age
- on open skin wounds

When using this product keep out of eyes, ears, and mouth. In case of contact with eyes, rinse eyes thoroughly with water.
Stop use and ask a doctor if irritation or rash occurs. These may be signs of a serious condition.
Keep out of reach of children. If swallowed, get medical help or contact a Poison Control Center right away.

Stop use and ask a doctor if irritation or rash occurs. These may be signs of a serious condition.

Keep out of reach of children. If swallowed, get medical help or contact a Poison Control Center right away.

Directions

- Place enough product on hands to cover all surfaces. Rub hands together until dry.
- Supervise children under 6 years of age when using this product to avoid swallowing.

Other information

Store between 59-86F (15-30C)
Avoid freezing and excessive heat above 104F (40C)
May discolor certain fabrics or surfaces

Inactive ingredients

glycerin, hydrogen peroxide, purified water USP, acrylate, copolymer

Package Label - Principal Display Panel

57 mL NDC: 78299-142-11